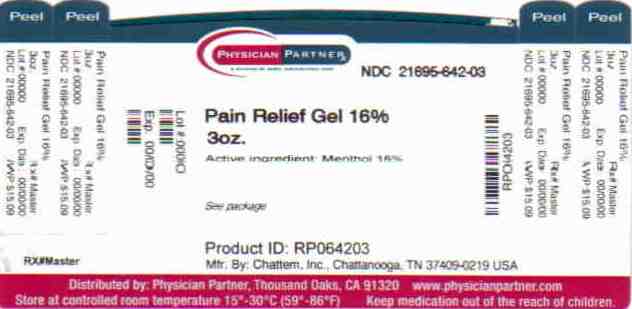 DRUG LABEL: Flexall Pain Relieving
NDC: 21695-642 | Form: GEL
Manufacturer: Rebel Distributors Corp
Category: otc | Type: HUMAN OTC DRUG LABEL
Date: 20110209

ACTIVE INGREDIENTS: MENTHOL 0.16 g/1 g
INACTIVE INGREDIENTS: ALLANTOIN; ALOE VERA LEAF; DIISOPROPYL ADIPATE; GLYCERIN; PEPPERMINT OIL; METHYL SALICYLATE; STEARETH-2; STEARETH-21; THYME OIL; .ALPHA.-TOCOPHEROL ACETATE, D-; TROLAMINE; WATER

Flexall Max

Drug Facts

Active ingredient

Menthol 16%

Purpose

Topical analgesic

Uses

temporarily relieves minor pain associated with:

- arthritis
- simple backache
- muscle strains
- sprains
- bruises
- cramps

Warnings

For external use only

Allergy alert:

do not use

if you are allergic to salicylates (including aspirin) unless directed by a doctor.

When using this product

- use only as directed
- do not bandage tightly or use with a heating pad
- avoid contact with eyes and mucous membranes
- do not apply to wounds or damaged, broken or irritated skin

Stop use and ask a doctor if

- condition worsens
- redness is present
- irritation develops
- symptoms persist for more than 7 days or clear up and occur again within a few days

If pregnant or breast-feeding,

ask a health professional before use.

Keep out of reach of children.

If swallowed, get medical help or contact a Poison Control Center right away.

Directions

adults and children over 12 years:

- apply generously to affected area
- massage into painful area until thoroughly absorbed into skin
- repeat as necessary, but no more than 3 to 4 times daily

children 12 years or younger: ask a doctor

Inactive ingredients

allantoin, aloe barbadensis leaf juice, carbomer, diisopropyl adipate, eucalyptus globulus leaf oil, glycerin, mentha piperita (peppermint) oil, methyl salicylate, SD alcohol 40 (15% w/w), steareth-2, steareth-21, thymus vulgaris (thyme) oil, tocopheryl acetate, triethanolamine, water (234-166)

PRINCIPAL DISPLAY PANEL

Maximum Strength
Flexall®
Pain Relieving Gel In An Aloe Vera Base
Menthol 16%
Net wt 3 oz (85 g)